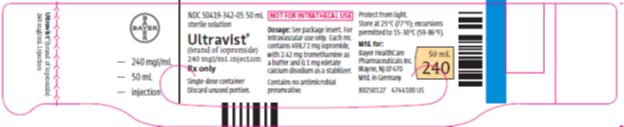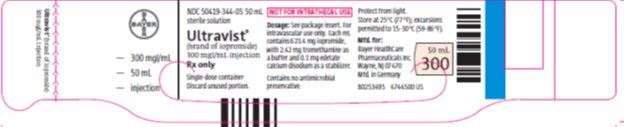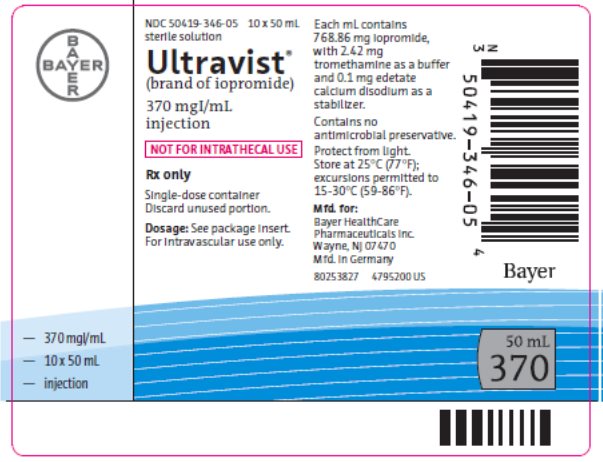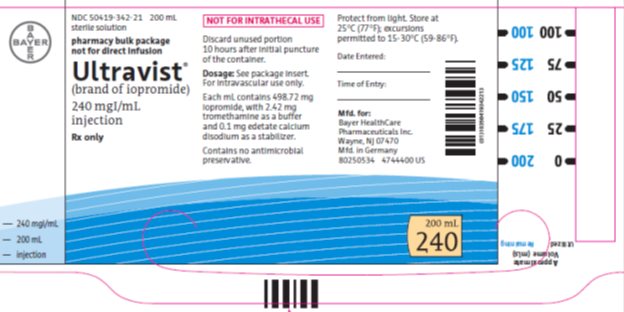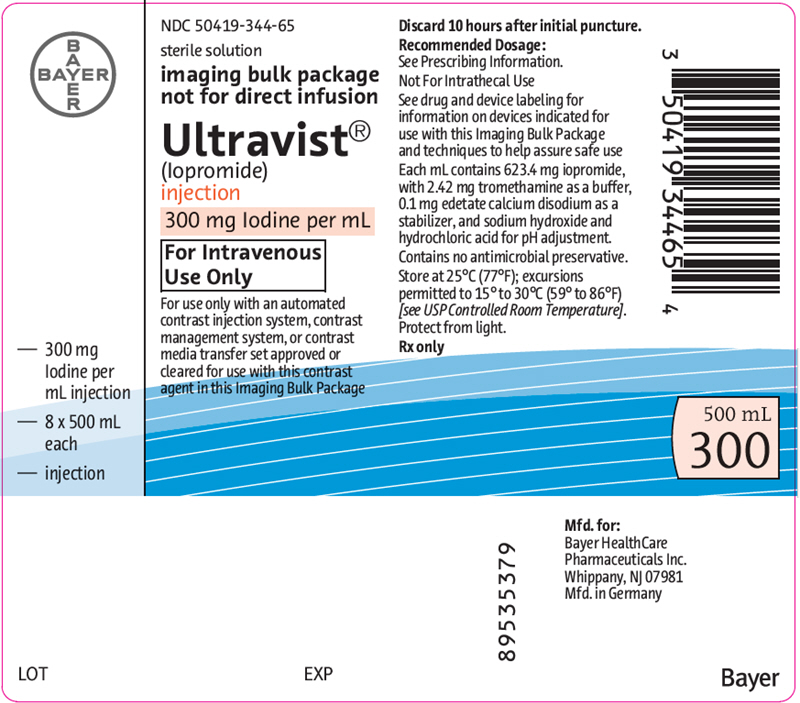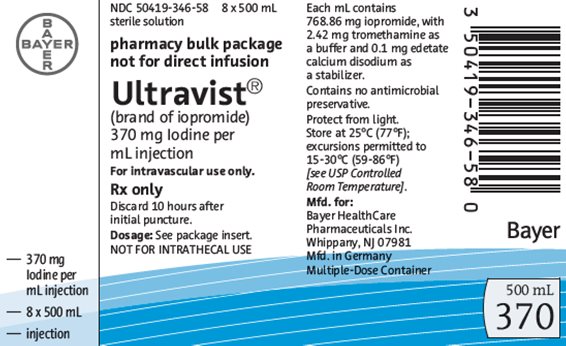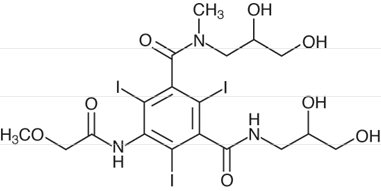 DRUG LABEL: Ultravist
NDC: 50419-342 | Form: INJECTION
Manufacturer: Bayer HealthCare Pharmaceuticals Inc.
Category: prescription | Type: HUMAN PRESCRIPTION DRUG LABEL
Date: 20250814

ACTIVE INGREDIENTS: IOPROMIDE 240 mg/1 mL
INACTIVE INGREDIENTS: EDETATE CALCIUM DISODIUM; TROMETHAMINE; SODIUM HYDROXIDE; HYDROCHLORIC ACID

HIGHLIGHTS OF PRESCRIBING INFORMATION

These highlights do not include all the information needed to use ULTRAVIST Injection safely and effectively. See full prescribing information for ULTRAVIST Injection.
ULTRAVIST (iopromide) Injection, for intravenous or intra-arterial use
Initial U.S. Approval: 1995

RECENT MAJOR CHANGES

Indications and Usage (1.2) 5/2023

Dosage and Administration (2.3, 2.5) 5/2023

Warning and Precautions (5.8) 4/2023

WARNING: NOT FOR INTRATHECAL USE

See full prescribing information for complete boxed warning.

Intrathecal administration, even if inadvertent, may cause death, convulsions, cerebral hemorrhage, coma, paralysis, arachnoiditis, acute renal failure, cardiac arrest, seizures, rhabdomyolysis, hyperthermia, and brain edema. ULTRAVIST is not approved for intrathecal use. (5.1)

1 INDICATIONS AND USAGE

ULTRAVIST is a radiographic contrast agent indicated for:

Intra-Arterial Procedures†

- Cerebral arteriography and peripheral arteriography in adults (1.1)
- Coronary arteriography and left ventriculography, visceral angiography, and aortography in adults (1.1)
- Radiographic evaluation of cardiac chambers and related arteries in pediatric patients aged 2 years and older (1.1)

Intravenous Procedures†

- Excretory urography in adults and pediatric patients aged 2 years and older (1.2)
- Contrast computed tomography (CT) of head and body in adults and pediatric patients aged 2 years and older (1.2)
- Contrast mammography in adults as an adjunct following mammography and/or ultrasound (1.2)

†Specific concentrations and presentations are recommended for each type of imaging procedure. (2.2, 2.3, 2.4)

2 DOSAGE AND ADMINISTRATION

- Individualize the volume and concentration according to the specific dosing tables accounting for factors such as age, body weight, size of the vessel, and the rate of blood flow within the vessel. (2.2, 2.3, 2.4)
- For contrast mammography, use ULTRAVIST with a device that is cleared for dual-energy full field digital mammography. (2.5)
- See full prescribing information for important dosage and administration instructions and directions for use of pharmacy bulk packages and imaging bulk packages. (2.1, 2.6, 2.7)

3 DOSAGE FORMS AND STRENGTHS

Injection: 300 mg Iodine per mL and 370 mg Iodine per mL in single-dose vials, pharmacy bulk packages, and imaging bulk packages. (3)

4 CONTRAINDICATIONS

None

5 WARNINGS AND PRECAUTIONS

- Hypersensitivity Reactions: Life-threatening or fatal reactions can occur. Always have emergency equipment and trained personnel available. (5.2)
- Acute Kidney Injury: Acute injury including renal failure can occur. Dose minimization and hydration may decrease risk. (5.3)
- Cardiovascular Reactions: Hemodynamic disturbances including shock and cardiac arrest may occur during or after administration. (5.4)
- Thyroid Dysfunction in Pediatric Patients 0 to 3 Years of Age: Individualize thyroid function monitoring based on risk factors such as prematurity (5.8)

6 ADVERSE REACTIONS

Common adverse reactions (>1%) are headache, nausea, injection site and infusion site reactions, vasodilatation, vomiting, back pain, urinary urgency, chest pain, pain, dysgeusia, and abnormal vision. (6)

To report SUSPECTED ADVERSE REACTIONS, contact Bayer HealthCare Pharmaceuticals Inc. at 1-888-842-2937 or FDA at 1-800-FDA-1088 or www.fda.gov/medwatch.

FULL PRESCRIBING INFORMATION

1 INDICATIONS AND USAGE

ULTRAVIST® Injection is an iodinated contrast agent indicated for:

1.1 Intra-Arterial Procedures*

ULTRAVIST is indicated for:

- Cerebral arteriography and peripheral arteriography in adults
- Coronary arteriography and left ventriculography, visceral angiography, and aortography in adults
- Radiographic evaluation of cardiac chambers and related arteries in pediatric patients aged 2 years and older

1.2 Intravenous Procedures*

ULTRAVIST is indicated for:

- Excretory urography in adults and pediatric patients aged 2 years and older
- Contrast Computed Tomography (CT) of the head and body (intrathoracic, intra-abdominal, and retroperitoneal regions) for the evaluation of neoplastic and non-neoplastic lesions in adults and pediatric patients aged 2 years and older
- Contrast mammography to visualize known or suspected lesions of the breast in adults, as an adjunct following mammography and/or ultrasound

†Specific concentrations and presentations of ULTRAVIST are recommended for each type of imaging procedure [see Dosage and Administration (2.2, 2.3, 2.4)].

2 DOSAGE AND ADMINISTRATION

2.1 Important Dosage and Administration Information

- ULTRAVIST is for intra-arterial or intravenous use only and must not be administered intrathecally [see Warnings and Precautions (5.1)].
- Specific concentrations and presentations of ULTRAVIST are recommended for each type of imaging procedure [see Dosage and Administrations (2.2, 2.3, 2.4)].
- Hydrate patients, as appropriate, prior to and following the administration of ULTRAVIST [see Warnings and Precautions (5.3)].
- Individualize the volume, concentration, and injection rate of ULTRAVIST according to the specific dosing tables [see Dosage and Administration (2.2, 2.3, 2.4)]. Consider factors such as age, body weight, size of the vessel, and the rate of blood flow within the vessel; also consider extent of opacification required, structure(s) or area to be examined, disease processes affecting the patient, and equipment and technique to be employed.
- Visually inspect ULTRAVIST for particulate matter and/or discoloration, whenever solution and container permit. Do not administer ULTRAVIST if particulate matter (including crystals) and/or discoloration is observed or if containers are defective.
- Use aseptic technique for all handling and administration of ULTRAVIST.
- Warm ULTRAVIST to body temperature before administration.
- ULTRAVIST can be used with 0.9% Sodium Chloride Injection in a power injector suitable for simultaneous injection of contrast [see Dosage and Administration (2.3)]. However, do not mix or inject ULTRAVIST in intravenous administration lines containing other drugs or total nutritional admixtures.
- Discard any unused portion remaining in the single-dose container following initial use.

2.2 Recommended Dosage for Intra-Arterial Procedures in Adults

- The recommended doses for intra-arterial procedures in adults are shown in Table 1.
- Inject at rates approximately equal to the flow rate in the vessel being injected.

Table 1: Recommended Concentrations and Volume of ULTRAVIST to Administer per Single Injection for Selected Injection Sites of Intra-Arterial Procedures in Adults
Imaging Procedure |  | Cerebral Arteriography | Peripheral Arteriography | Coronary Arteriography; and Left Ventriculography | Visceral Angiography; and; Aortography
Concentration; (mg Iodine per mL) |  | 300* | 300* | 370* | 370*
Intra-Arterial Injection Sites | Carotid Arteries | 3 mL to 12 mL | - | - | -
Intra-Arterial Injection Sites | Vertebral Arteries | 4 mL to 12 mL | - | - | -
Intra-Arterial Injection Sites | Aortic Arch Injection (four vessel study) | 20 mL to 50 mL | - | - | -
Intra-Arterial Injection Sites | Subclavian or Femoral Artery | - | 5 mL to 40 mL | - | -
Intra-Arterial Injection Sites | Aortic Bifurcation (distal runoff) | - | 25 mL to 50 mL | - | -
Intra-Arterial Injection Sites | Right Coronary Artery | - | - | 3 mL to 14 mL | -
Intra-Arterial Injection Sites | Left Coronary Artery | - | - | 3 mL to 14 mL | -
Intra-Arterial Injection Sites | Left Ventricle | - | - | 30 mL to 60 mL | -
Intra-Arterial Injection Sites | Aorta and Major Abdominal Branches | - | - | - | Individualize a volume approximately equal to the blood flow and related to the vascular and pathological characteristics of the specific vessels being studied.
Maximum Total Dose |  | 150 mL | 250 mL | 225 mL | 225 mL

*Use single-dose vials or pharmacy bulk package.

2.3 Recommended Dosage for Intravenous Procedures in Adults

Recommended doses for intravenous procedures in adults are shown in Table 2.

Table 2: Recommended Concentrations and Volume of ULTRAVIST for Intravenous Procedures in Adults
Imaging Procedure | Excretory Urography | Contrast Computed Tomography |  | Contrast Mammography
Concentration; (mg Iodine per mL) | 300* | 300‡ | 370‡ | 300‡ or 370‡
Excretory Urography | 1 mL/kg body weight | - | - | -
CT of Head | - | 50 mL to 200 mL | 41 mL to 162 mL | -
CT of Body - Single Phase Contrast; Bolus Injection; Rapid Infusion | - | 50 mL to 200 mL; 100 mL to 200 mL | 41 mL to 162 mL; 81 mL to 162 mL | -
CT of Body – Multiple Phase Contrast | - | 50 mL to 200 mL total volume; Phase 1: 100% contrast,; Phase 2: 20% to 60% contrast,; using a power injector suitable for simultaneous injection of contrast and 0.9% Sodium Chloride Injection | 41 mL to 162 mL total volume; Phase 1: 100% contrast,; Phase 2: 20% to 60% contrast,; using a power injector suitable for simultaneous injection of contrast and 0.9% Sodium Chloride Injection | -
Contrast Mammography | - | - | - | 1.5 mL/kg body weight using a power injector at 2 mL/second to 4 mL/second
Maximum Total Dose | 100 mL | 200 mL | 162 mL | 150 mL

*Use single-dose vials or pharmacy bulk package.
‡Use single-dose vials, pharmacy bulk package or imaging bulk package.

2.4 Recommended Dosage in Pediatric Patients Aged 2 Years and Older

The recommended doses in pediatric patients aged 2 years and older are shown in Table 3.

Table 3: Recommended Concentrations and Volume per Body Weight of ULTRAVIST for Cardiac Chambers and Related Arteries, Excretory Urography, and Contrast Computed Tomography in Pediatric Patients Aged 2 Years and Older
Imaging Procedure | Intra-arterial | Intravenous
Imaging Procedure | Cardiac Chambers and Related Arteries | Excretory Urography | Contrast Computerized Tomography
Concentration; (mg Iodine/mL) | 370* | 300* | 300‡
Volume; (mL/kg body weight) | 1 to 2 | 1 to 2 | 1 to 2
Maximum Total Dose (mL/kg) | 4 | 3 | 3

*Use single-dose vials or pharmacy bulk package.
‡Use single-dose vials, pharmacy bulk package or imaging bulk package.

2.5 Imaging Instruction for Contrast Mammography

For contrast mammography, use ULTRAVIST with a device that is cleared for dual-energy full field digital mammography.

2.6 Directions for Use of ULTRAVIST Pharmacy Bulk Package

- ULTRAVIST Pharmacy Bulk Package (PBP) is not for direct infusion.
- Perform the transfer of the PBP in a suitable work area, such as a laminar flow hood, utilizing aseptic technique.
- Penetrate the container closure only one time, utilizing a suitable transfer device.
- After initial puncture, use the contents of the PBP within 10 hours. Discard any unused portion

2.7 Directions for Use of ULTRAVIST Imaging Bulk Package

- ULTRAVIST Imaging Bulk Package (IBP) is for intravenous use only.
- ULTRAVIST IBP is for use only with an automated contrast injection system, contrast management system, or contrast media transfer set approved or cleared for use with this contrast agent in this IBP. Please see drug and device labeling for information on devices indicated for use with this IBP and techniques to help assure safe use.
- The IBP is to be used only in a room designated for radiological procedures that involve intravascular administration of a contrast agent.
- Using aseptic technique, penetrate the container closure of the IBP only one time with a suitable sterile component of the automated contrast injection system, contrast management system, or contrast media transfer set approved or cleared for use with this contrast agent in this IBP.
- Once the IBP is punctured, do not remove it from the work area during the entire period of use. Maintain the bottle in an inverted position such that container contents are in continuous contact with the dispensing set.
- After the container closure is punctured, if the integrity of the IBP and the delivery system cannot be assured through direct continuous supervision, discard the IBP and all associated disposables for the automated contrast injection system, contrast management system, or contrast media transfer set.
- A maximum use time from initial puncture is 10 hours. Discard any unused portion remaining in IBP container.
- Storage temperature of IBP after the closure has been entered should not exceed 25°C (77°F) with excursions permitted to 15°C to 30°C (59°F to 86°F); however, it is desirable that the contents be warmed to body temperature prior to injection.

3 DOSAGE FORMS AND STRENGTHS

ULTRAVIST injection is a clear, colorless to slightly yellow, odorless solution available in two concentrations:

300 mg Iodine per mL available as

- 50 mL, 100 mL, 125 mL, and 150 mL in single-dose vials
- 200 mL and 500 mL in pharmacy bulk packages
- 200 mL and 500 mL in imaging bulk packages

370 mg Iodine per mL available as

- 50 mL, 100 mL, 125 mL, and 150 mL in single-dose vials
- 200 mL and 500 mL in pharmacy bulk packages
- 200 mL and 500 mL in imaging bulk packages

4 CONTRAINDICATIONS

None

5 WARNINGS AND PRECAUTIONS

5.1 Risks Associated with Intrathecal Use

Intrathecal administration, even if inadvertent, can cause death, convulsions, cerebral hemorrhage, coma, paralysis, arachnoiditis, acute renal failure, cardiac arrest, seizures, rhabdomyolysis, hyperthermia, and brain edema. ULTRAVIST is for intra-arterial or intravenous use only [see Dosage and Administration (2.2, 2.3, 2.4)]. ULTRAVIST is not approved for intrathecal use.

5.2 Hypersensitivity Reactions

ULTRAVIST can cause life-threatening or fatal hypersensitivity reactions including anaphylaxis. Manifestations include respiratory arrest, laryngospasm, bronchospasm, angioedema, and shock [see Adverse Reactions (6.2)]. Most severe reactions develop shortly after the start of injection (e.g., within 1 to 3 minutes), but delayed reactions can also occur. There is increased risk of hypersensitivity reactions in patients with a history of previous reaction to a contrast agent and known allergic disorders (that is, bronchial asthma, allergic rhinitis, and food allergies), or other hypersensitivities. Premedication with antihistamines or corticosteroids does not prevent serious life-threatening reactions but may reduce both their incidence and severity.

Obtain a history of allergy, hypersensitivity, or hypersensitivity reactions to iodinated contrast agents and have emergency resuscitation equipment and trained personnel available prior to ULTRAVIST administration. Monitor all patients for hypersensitivity reactions.

5.3 Acute Kidney Injury

Acute kidney injury, including renal failure, may occur after administration of ULTRAVIST. Risk factors include: pre-existing renal insufficiency, dehydration, diabetes mellitus, congestive heart failure, advanced vascular disease, elderly age, concomitant use of nephrotoxic or diuretic medications, multiple myeloma or other paraproteinemia, and repetitive and/or large doses of ULTRAVIST.

Use the lowest necessary dose of ULTRAVIST in patients with renal impairment. Hydrate patients prior to and following ULTRAVIST administration. Do not use laxatives, diuretics, or preparatory dehydration prior to ULTRAVIST administration.

5.4 Cardiovascular Adverse Reactions

ULTRAVIST increases the circulatory osmotic load and may induce acute or delayed hemodynamic disturbances in patients with congestive heart failure, severely impaired renal function, combined renal and hepatic disease, or combined renal and cardiac disease, particularly when repetitive and/or large doses are administered. Fatal cardiovascular reactions have occurred mostly within 10 minutes of ULTRAVIST injection; the main feature was cardiac arrest with cardiovascular disease as the main underlying factor. Hypotensive collapse and shock have occurred. Cardiac decompensation, serious arrhythmias, and myocardial ischemia or infarction can occur during coronary arteriography and ventriculography.

The administration of ULTRAVIST may cause pulmonary edema in patients with heart failure. Based upon published reports, deaths from the administration of iodinated contrast agents range from 6.6 per 1 million (0.00066 percent) to 1 in 10,000 patients (0.01 percent). Use the lowest necessary dose of ULTRAVIST in patients with congestive heart failure and always have emergency resuscitation equipment and trained personnel available. Monitor all patients for severe cardiovascular reactions.

5.5 Thromboembolic Events

angiography procedures. During these procedures, increased thrombosis and activation of the complement system can occur. Risk of thromboembolic events can be influenced by: length of procedure, catheter and syringe material, underlying disease state, and concomitant medications.

To decrease thromboembolic events, use meticulous angiographic techniques and minimize the length of the procedure. Avoid blood remaining in contact with syringes containing iodinated contrast agents, which increases the risk of clotting. Avoid angiography in patients with homocystinura because of the risk of inducing thrombosis and embolism.

5.6 Extravasation and Injection Site Reactions

Extravasation can occur with ULTRAVIST, particularly in patients with severe arterial or venous disease. Inflammation, blistering, skin necrosis, and compartment syndrome have been reported following extravasation. In addition, injection site reactions such as pain and swelling at the injection site can also occur [see Adverse Reactions (6.1)]. Ensure intravascular placement of catheters prior to injection. Monitor patients for extravasation and advise patients to seek medical care for progression of symptoms.

5.7 Thyroid Storm in Patients with Hyperthyroidism

Thyroid storm has occurred after the intravascular use of iodinated contrast agents in patients with hyperthyroidism or with an autonomously functioning thyroid nodule. Evaluate the risk in such patients before use of ULTRAVIST.

5.8 Thyroid Dysfunction in Pediatric Patients 0 to 3 Years of Age

Thyroid dysfunction characterized by hypothyroidism or transient thyroid suppression has been reported after both single exposure and multiple exposures to iodinated contrast media (ICM) in pediatric patients 0 to 3 years of age.

Younger age, very low birth weight, prematurity, underlying medical conditions affecting thyroid function, admission to neonatal or pediatric intensive care units, and congenital cardiac conditions are associated with an increased risk of hypothyroidism after ICM exposure. Pediatric patients with congenital cardiac conditions may be at the greatest risk given that they often require high doses of contrast during invasive cardiac procedures.

An underactive thyroid during early life may be harmful for cognitive and neurological development and may require thyroid hormone replacement therapy. After exposure to ICM, individualize thyroid function monitoring based on underlying risk factors, especially in term and preterm neonates.

The safety and effectiveness of ULTRAVIST in pediatric patients younger than 2 years of age have not been established, and ULTRAVIST is not approved for use in pediatric patients younger than 2 years of age [see Use in Specific Populations (8.4)].

5.9 Hypertensive Crisis in Patients with Pheochromocytoma

Hypertensive crisis in patients with pheochromocytoma has occurred with iodinated contrast agents. Closely monitor patients when administering ULTRAVIST if pheochromocytoma or catecholamine-secreting paragangliomas are suspected. Inject the minimum amount of ULTRAVIST necessary and have measures for treatment of a hypertensive crisis readily available.

5.10 Sickle Cell Crisis in Patients with Sickle Cell Disease

Iodinated contrast agents may promote sickling in individuals who are homozygous for sickle cell disease. Hydrate patients prior to and following ULTRAVIST administration and use only if the necessary imaging information cannot be obtained with alternative imaging modalities.

5.11 Severe Cutaneous Adverse Reactions

Severe cutaneous adverse reactions (SCAR) may develop from 1 hour to several weeks after intravascular contrast agent administration. These reactions include Stevens-Johnson syndrome and toxic epidermal necrolysis (SJS/TEN), acute generalized exanthematous pustulosis (AGEP), and drug reaction with eosinophilia and systemic symptoms (DRESS). Reaction severity may increase and time to onset may decrease with repeat administration of contrast agent; prophylactic medications may not prevent or mitigate severe cutaneous adverse reactions. Avoid administering ULTRAVIST to patients with a history of a severe cutaneous adverse reaction to ULTRAVIST.

5.12 Interference with Laboratory Tests

ULTRAVIST can interfere with protein-bound iodine test [see Drug Interactions (7.2)].

6 ADVERSE REACTIONS

The following adverse reactions are described elsewhere in the labeling:

- Risks Associated with Intrathecal Use [see Warnings and Precautions (5.1)]
- Hypersensitivity Reactions [see Warnings and Precautions (5.2)]
- Acute Kidney Injury [see Warnings and Precautions (5.3)]
- Cardiovascular Adverse Reactions [see Warnings and Precautions (5.4)]
- Thromboembolic Events [see Warnings and Precautions (5.5)]
- Extravasation and Injection Site Reactions [see Warnings and Precautions (5.6)]
- Thyroid Dysfunction in Pediatric Patients 0 to 3 Years of Age [see Warnings and Precautions (5.8)]
- Severe Cutaneous Adverse Reactions [see Warnings and Precautions (5.11)]

6.1 Clinical Trials Experience

Because clinical trials are conducted under widely varying conditions, adverse reaction rates observed in the clinical trials of a drug cannot be directly compared to rates in the clinical trials of another drug and may not reflect or predict the rates observed in practice.

The common adverse reactions reported in >1% of patients in clinical studies with ULTRAVIST are shown in Table 4.

Table 4: Adverse Reactions Reported in >1% of Patients Receiving ULTRAVIST in Clinical Trials
System Organ Class | Adverse Reaction | ULTRAVIST
System Organ Class | Adverse Reaction | N=1,142 (%)
Nervous system disorders | Headache | 46 (4)
Nervous system disorders | Dysgeusia | 15 (1.3)
Eye disorders | Abnormal Vision | 12 (1.1)
Cardiac disorders | Chest pain | 18 (1.6)
Vascular disorders | Vasodilatation | 30 (2.6)
Gastrointestinal disorders | Nausea | 42 (3.7)
Gastrointestinal disorders | Vomiting | 22 (1.9)
Musculoskeletal and connective tissue disorders | Back pain | 22 (1.9)
Renal and urinary disorders | Urinary urgency | 21 (1.8)
General disorders and administration site conditions | Injection site and infusion site reactions (hemorrhage, hematoma, pain, edema, erythema, rash) | 41 (3.7)
General disorders and administration site conditions | Pain | 13 (1.4)

One or more adverse reactions were recorded in 273 of 1,142 (24%) patients during the clinical trials, coincident with the administration of ULTRAVIST or within the defined duration of the study follow-up period (24–72 hours). ULTRAVIST is often associated with sensations of warmth and/or pain.

Serious, life-threatening, and fatal reactions have been associated with the administration of iodine-containing contrast media, including ULTRAVIST. In clinical trials 7 of 1,142 patients given ULTRAVIST died 5 days or later after drug administration. Also, 10 of 1,142 patients given ULTRAVIST had serious adverse events.

The following adverse reactions were observed in ≤1% of the patients receiving ULTRAVIST:

Cardiac disorders:

atrioventricular block (complete), bradycardia, ventricular extrasystole

Gastrointestinal disorders:

abdominal discomfort, abdominal pain, abdominal pain upper, constipation, diarrhea, dry mouth, dyspepsia, gastrointestinal disorder, gastrointestinal pain, salivation increased, stomach discomfort, rectal tenesmus

General disorders and administration site conditions:

asthenia, chest discomfort, chills, excessive thirst, extravasation, feeling hot, hyperhidrosis, malaise, edema peripheral, pyrexia

Immune system disorders:

asthma, face edema

Investigations:

blood lactate dehydrogenase increased, blood urea increased, hemoglobin increased, white blood cell count increased

Musculoskeletal and connective tissue disorders:

arthralgia, musculoskeletal pain, myasthenia, neck pain, pain in extremity

Nervous system disorders:

agitation, confusion, convulsion, dizziness, hypertonia, hypesthesia, incoordination, neuropathy, somnolence, speech disorder, tremor, paresthesia, visual field defect

Psychiatric disorders:

anxiety

Renal and urinary disorders:

dysuria, renal pain, urinary retention

Respiratory, thoracic and mediastinal disorders:

apnea, cough increased, dyspnea, hypoxia, pharyngeal edema, pharyngitis, pleural effusion, pulmonary hypertension, respiratory disorder, sore throat

Skin and subcutaneous tissue disorders:

erythema, pruritus, rash, urticaria

Vascular disorders:

coronary artery thrombosis, flushing, hypertension, hypotension, peripheral vascular disorder, syncope, vascular anomaly

Pediatric Patients

A total of 274 pediatric patients were evaluated with intra-arterial coronary angiography (n=60), intravenous contrast computerized tomography (CT) (n=87), excretory urography (n=99), and 28 other procedures. These patients received 1 mL/kg to 2 mL/kg body weight of a concentration of 300 mg Iodine per mL for intravenous contrast CT or excretory urography and 370 mg Iodine per mL for intra-arterial and intracardiac administration in the radiographic evaluation of the heart cavities and major arteries [see Dosage and Administration (2.4)]. Among these, 131 were 2 to 12 years old, 57 were adolescents, and 86 were unreported or other ages. There were 148 females, 94 males, and 32 in whom gender was not reported. The racial distribution was: White 33.9%, Black 0.4%, Asian 2.2%, and unknown 63.5%. The overall character, quality, and severity of adverse reactions in pediatric patients are generally similar to those reported in adult patients.

6.2 Postmarketing Experience

The following adverse reactions have been identified during post approval use of ULTRAVIST. Because these reactions are reported voluntarily from a population of uncertain size, it is not always possible to reliably estimate their frequency or establish a causal relationship to drug exposure. Adverse reactions reported in foreign postmarketing surveillance and other trials with the use of ULTRAVIST include:

Cardiac disorders:

cardiac arrest, ventricular fibrillation, atrial fibrillation, tachycardia, palpitations, congestive heart failure, myocardial infarction, angina pectoris

Ear and labyrinth disorders:

vertigo, tinnitus

Endocrine disorders:

hyperthyroidism, thyrotoxic crisis, hypothyroidism

Eye disorders:

mydriasis, lacrimation disorder

Gastrointestinal disorders:

dysphagia, swelling of salivary glands

Immune system disorders:

anaphylactoid reaction (including fatal cases), respiratory arrest, anaphylactoid shock, angioedema, laryngeal edema, laryngospasm, bronchospasm, hypersensitivity

Musculoskeletal and connective tissue disorders:

compartment syndrome in case of extravasation

Nervous system disorders:

cerebral ischemia/infarction, paralysis, paresis, transient cortical blindness, aphasia, coma, unconsciousness, amnesia, hypotonia, aggravation of myasthenia gravis symptoms

Renal and urinary disorders:

renal failure, hematuria

Respiratory, thoracic and mediastinal disorders:

pulmonary edema, acute respiratory distress syndrome, asthma

Skin and subcutaneous tissue disorders:

Reactions range from mild (e.g., rash, erythema, pruritus, urticaria and skin discoloration) to severe [e.g., Stevens-Johnson Syndrome and toxic epidermal necrolysis (SJS/TEN), acute generalized exanthematous pustulosis (AGEP), and drug reaction with eosinophilia and systemic symptoms (DRESS)].

Vascular disorders:

vasospasm

Pediatric Patients

Additional adverse reactions reported in pediatric patients from foreign marketing surveillance or other information include: epistaxis, migraine, joint disorder (effusion), muscle cramps, mucous membrane disorder (mucosal swelling), conjunctivitis, fixed eruptions, diabetes insipidus, and brain edema.

6.3 Pediatrics

The overall character, quality, and severity of adverse reactions in pediatric patients are generally similar to those reported in adult patients. Additional adverse reactions reported in pediatric patients from foreign marketing surveillance or other information are: epistaxis, angioedema, migraine, joint disorder (effusion), muscle cramps, mucous membrane disorder (mucosal swelling), conjunctivitis, hypoxia, fixed eruptions, vertigo, diabetes insipidus, and brain edema [see Use in Specific Populations (8.4)].

7 DRUG INTERACTIONS

7.1 Drug-Drug Interactions

Metformin

In patients with renal impairment, biguanides can cause lactic acidosis. Iodinated contrast agents appear to increase the risk of metformin-induced lactic acidosis, possibly as a result of worsening renal function. Stop metformin at the time of, or prior to, ULTRAVIST administration in patients with an eGFR between 30 and 60 mL/min/1.73 m2; in patients with a history of hepatic impairment, alcoholism, or heart failure; or in patients who will be administered intra-arterial iodinated contrast agents. Re-evaluate eGFR 48 hours after the imaging procedure and reinstitute only after renal function is stable.

Radioactive Iodine

ULTRAVIST may interfere with thyroid uptake of radioactive iodine (I-131 and I-123) and decrease therapeutic and diagnostic efficacy. Avoid thyroid therapy or testing for up to 6 weeks post ULTRAVIST.

7.2 Drug-Laboratory Test Interactions

Protein-Bound Iodine Test

Iodinated contrast agents, including ULTRAVIST, will temporarily increase protein-bound iodine in blood. Do not perform protein-bound iodine test for at least 16 days following administration of ULTRAVIST. However, thyroid function tests which do not depend on iodine estimations, for example, T3 resin uptake and total or free thyroxine (T4) assays are not affected.

8 USE IN SPECIFIC POPULATIONS

8.1 Pregnancy

Risk Summary

There are no data on ULTRAVIST use in pregnant women to evaluate for a drug-associated risk of major birth defects, miscarriage, or adverse maternal or fetal outcomes. Iopromide crosses the placenta and reaches fetal tissues in small amounts (see Data). In animal reproduction studies, intravenous administration of iopromide to pregnant rats and rabbits during organogenesis at doses up to0.35 and 0.7 times, respectively, the maximum recommended human dose based on body surface area resulted in no relevant adverse developmental effects (see Data).

The estimated background risk of major birth defects and miscarriage for the indicated population is unknown. All pregnancies have a background risk of birth defects, loss, or other adverse outcomes. In the U.S. general population, the estimated background risk of major birth defects and miscarriage in clinically recognized pregnancies is 2% to 4% and 15% to 20%, respectively.

Data

Human Data

Limited case reports demonstrate that intravenously administered iodinated contrast agents, including iopromide, cross the placenta and are visualized in the digestive tract of exposed infants after birth.

Animal Data

Reproduction studies were performed with intravenous iopromide in rats (day 6 to 15 of gestation) and rabbits (day 6 to 18 of gestation) at dose levels of 0, 0.37, 1.11, and 3.7 g iodine per kg, corresponding to doses up to 0.35 times (rats) and 0.7 times (rabbits) the maximum human recommended dose based on body surface area. Iopromide was not teratogenic at any dose level in rats and rabbits and embryolethality was observed in rabbits that received 3.7 g iodine per kg, but this was considered to have been secondary to maternal toxicity.

8.2 Lactation

Risk Summary

There are no data on the presence of iopromide in human milk, the effects on the breastfed infant, or the effects on milk production. Iodinated contrast agents are poorly excreted into human milk and are poorly absorbed by the gastrointestinal tract of a breastfed infant. The developmental and health benefits of breastfeeding should be considered along with the mother's clinical need for ULTRAVIST and any potential adverse effects on the breastfed infant from ULTRAVIST or from the underlying maternal condition (see Clinical Considerations).

Clinical Considerations

Interruption of breastfeeding after exposure to iodinated contrast agents is not necessary because the potential exposure of the breastfed infant to iodine is small. However, a lactating woman may consider interrupting breastfeeding and pumping and discarding breast milk for 12 to 24 hours (approximately 5 elimination half-lives) after ULTRAVIST administration in order to minimize drug exposure to a breast fed infant.

8.4 Pediatric Use

The safety and efficacy of ULTRAVIST have been established in pediatric patients aged 2 years and older for radiographic evaluation of cardiac chambers and related arteries, excretory urography, and contrast computed tomography of head and body. Use of ULTRAVIST in these age groups for these indications is supported by evidence from adequate and well-controlled studies in adults and additional safety data in pediatric patients aged 2 years and older, including data from published studies [see Adverse Reactions (6.1, 6.2) and Clinical Studies (14.1, 14.2)].

Pediatric patients at higher risk of experiencing an adverse reaction during and after administration of any contrast agent include those with asthma, sensitivity to medication and/or allergens, cyanotic and acyanotic heart disease, congestive heart failure, or serum creatinine greater than 1.5 mg/dL.

Thyroid function tests indicative of thyroid dysfunction, characterized by hypothyroidism or transient thyroid suppression have been reported following iodinated contrast media administration in pediatric patients, including term and preterm neonates; Some patients were treated for hypothyroidism. After exposure to iodinated contrast media, individualize thyroid function monitoring in pediatric patients 0 to 3 years of age based on underlying risk factors, especially in term and preterm neonates [see Warnings and Precautions (5.8) and Adverse Reactions (6.2)].

Safety and effectiveness of ULTRAVIST have not been established in pediatric patients younger than 2 years for radiographic evaluation of cardiac chambers and related arteries, excretory urography, and contrast computed tomography of head and body.

Safety and effectiveness of ULTRAVIST for cerebral arteriography, peripheral arteriography, coronary arteriography and left ventriculography, visceral angiography, aortography, and contrast mammography have not been established in pediatric patients.

8.5 Geriatric Use

In a clinical study of ULTRAVIST for CT, 96/434 (22.1%) of patients were 65 and over. No overall differences in safety were observed between these patients and younger patients. Other reported clinical experience has not identified differences in response between the elderly and younger patients. Iopromide is known to be substantially excreted by the kidney, and the risk of adverse reactions to iopromide may be greater in patients with impaired renal function. Because elderly patients are more likely to have decreased renal function, care should be taken in dose selection, and it may be useful to monitor renal function.

8.6 Renal Impairment

The clearance of iopromide decreases with increasing degree of renal impairment and results in delayed opacification of the urinary system [see Clinical Pharmacology (12.3)]. In addition, preexisting renal impairment increases the risk for acute kidney injury [see Warnings and Precautions (5.3)]. Iopromide can be removed by dialysis.

10 OVERDOSAGE

The manifestations of overdosage are life-threatening and affect mainly the pulmonary and cardiovascular systems. Treatment of an overdosage is directed toward the support of all vital functions, and prompt institution of symptomatic therapy. Iopromide can be removed by dialysis.

11 DESCRIPTION

ULTRAVIST(iopromide) injection is a nonionic radiographic contrast agent for intra-arterial or intravenous administration. The chemical name for iopromide is N,N'-Bis(2,3-dihydroxypropyl)-2,4,6-triiodo-5-[(methoxyacetyl)amino]-N-methyl- 1,3- benzenedicarboxamide. Iopromide has a molecular weight of 791.12 (iodine content 48.12%).

Iopromide has the following structural formula:

Each mL contains 623.4 mg or 768.86 mg iopromide (300 mg or 370 mg iodine, respectively) and the following inactive ingredients: 0.1 mg edetate calcium disodium as a stabilizer and 2.42 mg tromethamine as a buffer. It may also contain sodium hydroxide or hydrochloric acid to adjust pH to 7.4 (6.5–8) at 25± 2°C and contains no preservatives.

ULTRAVIST is a sterile (sterilized by autoclaving), clear, colorless to slightly yellow, odorless, pyrogen-free aqueous solution and has the following physicochemical properties:

Property |  | Concentration of ULTRAVIST; (mg Iodine/mL)
Property |  | 300 | 370
Osmolality*(mOsmol/kg water) | @ 37°C | 607 | 774
Osmolarity*(mOsmol/L) | @ 37°C | 428 | 496
Viscosity (cP) | @ 20°C; @ 37°C | 9.2; 4.9 | 22; 10
Density (g/mL) | @ 20°C; @ 37°C | 1.330; 1.322 | 1.409; 1.399

*Osmolality was measured by vapor-pressure osmometry. Osmolarity was calculated from the measured osmolal concentrations.

ULTRAVIST 300 mg Iodine per mL and 370 mg Iodine per mL have osmolalities respectively 2.1 and 2.7 times that of plasma (285 mOsmol/kg water).

12 CLINICAL PHARMACOLOGY

12.1 Mechanism of Action

Intravascular injection of iopromide opacifies those vessels where the contrast agent is present, permitting radiographic visualization of the internal structures through attenuation of photons. In imaging of the body, iodinated contrast agents diffuse from the vessels into the extravascular space. In normal brain with an intact blood-brain barrier, contrast does not diffuse into the extravascular space. In patients with a disrupted blood-brain barrier, contrast agent accumulates in the extravascular space in the region of disruption.

12.2 Pharmacodynamics

Following ULTRAVIST administration, the degree of contrast enhancement is related to the iodine concentration in the tissue of interest.

12.3 Pharmacokinetics

Distribution

After intravenous administration to healthy adult subjects, plasma iopromide concentration time profile shows an initial distribution phase with a half-life of 0.24 hour; a main elimination phase with a half-life of 2 hours; and a terminal elimination phase with a half-life of 6.2 hours. The total volume of distribution at steady state is about 16 L suggesting distribution into extracellular space. Plasma protein binding of iopromide is 1%.

Iodinated contrast agents cross a disrupted blood-brain barrier.

Elimination

Metabolism

Iopromide does not undergo significant metabolism, deiodination, or biotransformation

Excretion

The amounts excreted unchanged in urine represent 97% of the dose in adult healthy subjects. Only 2% of the dose is recovered in the feces. Similar recoveries in urine and feces are observed in middle-aged and elderly patients. This finding suggests that, compared to the renal route, biliary and/or gastrointestinal excretion is not important for iopromide. During the slower terminal phase, only 3% of the dose is eliminated; 97% of the dose is disposed of during the earlier phases, the largest part of which occurs during the main elimination phase. The ratio of the renal clearance of iopromide to the creatinine clearance is 0.82 suggesting that iopromide is mainly excreted by glomerular filtration. Additional tubular reabsorption is possible. Pharmacokinetics of iopromide at intravenous doses up to 80 g iodine are dose proportionate and first order.

The mean total and renal clearances are 107 mL/min and 104 mL/min, respectively.

Specific Populations

Age

Middle-aged (49 to 64 years) and elderly patients (65 to 70 years), without significantly impaired renal function, who received ULTRAVIST in doses corresponding to 9–30 g iodine, had mean steady-state volumes of distribution that ranged between 30–40 L. Mean total and renal clearances were between 81–125 mL/min and 70–115 mL/min, respectively, in these patients, and were similar to the values found in the young subjects. The distribution phase half-life in this patient population was 0.1 hour, the main elimination phase half-life was 2.3 hours, and the terminal elimination phase half-life was 40 hours. The urinary excretion (97% of the dose) and fecal excretion (2%) were comparable to that observed in young healthy subjects, suggesting that, compared to the renal route, biliary and/or gastrointestinal excretion is not significant for iopromide.

Patients with Renal Impairment

A pharmacokinetic study in patients with mild (n=2), moderate (n=6), and severe (n=3) renal impairment was conducted. Mild and moderate patients had a CLCR between 30 to 80 mL/min/1.73 m^2. Severe patients had a CLCR between 10 to 30 mL/min/1.73 m^2. ULTRAVIST 300 mg Iodine per mL was administered intravenously using a single-dose bolus injection. The total clearance of iopromide was decreased proportionately to the baseline decrease in creatinine clearance. The plasma AUC increased about 2-fold in patients with moderate renal impairment and 6-fold in patients with severe renal impairment compared to subjects with normal renal function. The terminal half-life increased from 2.2 hours for subjects with normal renal function to 11.6 hours in patients with severe renal impairment. The peak plasma concentration of iopromide was not influenced by the extent of renal impairment [see Use in Specific Populations (8.6)].

13 NONCLINICAL TOXICOLOGY

13.1 Carcinogenesis, Mutagenesis, Impairment of Fertility

Long-term animal studies have not been performed with iopromide to evaluate carcinogenic potential or effects on fertility. Iopromide was not genotoxic in a series of studies including the Ames test, an in vitro human lymphocytes analysis of chromosomal aberrations, an in vivo mouse micro-nucleus assay, and in an in vivo mouse dominant lethal assay.

14 CLINICAL STUDIES

14.1 Overview of Clinical Studies

The following intra-arterial and intravenous procedures were studied with one of two concentrations of ULTRAVIST (300 mg Iodine per mL and 370 mg Iodine per mL): aortography/visceral angiography, coronary arteriography and left ventriculography, cerebral arteriography, peripheral arteriography, contrast computed tomography (CT) of head and body, excretory urography, and contrast mammography.

Efficacy assessment for most indications was based on the global evaluation of the quality of the images by rating visualization as either excellent, good, poor, or no image, and on the ability to make a diagnosis. For contrast mammography, efficacy assessment was based on rating visualized contrast uptake as negative, none, moderate, or intense.

14.2 Intra-Arterial Studies

Cerebral arteriography was evaluated in two randomized, double-blind clinical trials of ULTRAVIST 300 mg Iodine per mL in 80 patients with conditions such as altered cerebrovascular perfusion and/or permeability occurring in central nervous system diseases due to various CNS disorders. Visualization ratings were good or excellent in 99% of the patients with ULTRAVIST; a radiologic diagnosis was made in the majority of the patients. Confirmation of the radiologic findings by other diagnostic methods was not obtained.

Coronary arteriography/left ventriculography was evaluated in two randomized, double-blind clinical trials and one unblinded, unrandomized clinical trial of ULTRAVIST 370 mg Iodine per mL in 106 patients with conditions such as altered coronary artery perfusion due to metabolic causes and in patients with conditions such as altered ventricular function. Visualization ratings were good or excellent in 99% or more of the patients with ULTRAVIST; a radiologic diagnosis was made in the majority of the patients. Confirmation of the radiologic findings by other diagnostic methods was not obtained.

Aortography/visceral angiography was evaluated in two randomized, double-blind clinical trials of ULTRAVIST 370 mg Iodine per mL in 78 patients with conditions such as altered aortic blood flow and/or visceral vascular disorders. Visualization ratings were good or excellent in the majority of the patients with ULTRAVIST; a radiologic diagnosis was made in 99% of the patients. Confirmation of radiologic findings by other diagnostic methods was not obtained. The risks of renal arteriography could not be analyzed.

Similar studies were completed with comparable findings noted in peripheral arteriography.

14.3 Intravenous Studies

Contrast CT of head and body was evaluated in three randomized, double-blind clinical trials of ULTRAVIST 300 mg Iodine per mL in 95 patients with vascular disorders. Visualization ratings were good or excellent in 99% of the patients with ULTRAVIST; a radiologic diagnosis was made in the majority of the patients. Confirmation of contrast CT findings by other diagnostic methods was not obtained.

ULTRAVIST was evaluated in a blinded reader trial for CT of the head and body. Among the 382 patients who were evaluated with ULTRAVIST 370 mg Iodine per mL, visualization ratings were good or excellent in approximately 97% of patients.

Similar studies were completed with comparable findings noted in excretory urography.

Contrast mammography was evaluated in a published prospective study of 216 women (age range 26–85 years; mean age 54.6 years) who had BI-RADS 3, 4, or 5 findings on mammography and were evaluated using ULTRAVIST 300 mg Iodine per mL. Patients with breast implants, pregnancy or possible pregnancy, history of hypersensitivity reaction to iodinated contrast agents, and renal insufficiency were excluded from study. All breast lesions were evaluated in a blinded manner. A total of 226 lesions was evaluated, including 98 (43%) malignant lesions. Visualization of lesion contrast was scored on a 4-point scale, with 4 (2%) lesions rated as below background (negative), 93 (41%) as none, 46 (20%) as moderate, and 83 (37%) as intense.

16 HOW SUPPLIED/STORAGE AND HANDLING

How Supplied

ULTRAVIST injection is a sterile, clear, colorless to slightly yellow, odorless, pyrogen-free aqueous solution available in the following presentations:

ULTRAVIST 300 mg Iodine per mL
Package Type | Volume | Sale Unit | NDC
Single-Dose Vials | 50 mL | Carton of 10 | 50419-344-05
Single-Dose Vials | 100 mL | Carton of 10 | 50419-344-10
Single-Dose Vials | 125 mL | Carton of 10 | 50419-344-12
Single-Dose Vials | 150 mL | Carton of 10 | 50419-344-15
Pharmacy Bulk Package | 200 mL | Carton of 10 | 50419-344-21
Pharmacy Bulk Package | 500 mL | Carton of 8 | 50419-344-58
Imaging Bulk Package | 200 mL | Carton of 10 | 50419-344-23
Imaging Bulk Package | 500 mL | Carton of 8 | 50419-344-65
ULTRAVIST 370 mg Iodine per mL
Package Type | Volume | Sale Unit | NDC
Single-Dose Vials | 50 mL | Carton of 10 | 50419-346-05
Single-Dose Vials | 100 mL | Carton of 10 | 50419-346-10
Single-Dose Vials | 150 mL | Carton of 10 | 50419-346-15
Single-Dose Vials | 200 mL | Carton of 10 | 50419-346-20
Pharmacy Bulk Package | 200 mL | Carton of 10 | 50419-346-26
Pharmacy Bulk Package | 500 mL | Carton of 8 | 50419-346-58
Imaging Bulk Package | 200 mL | Carton of 10 | 50419-346-28
Imaging Bulk Package | 500 mL | Carton of 8 | 50419-346-65

Storage and Handling

Store at 25°C (77°F); excursions permitted to 15°C to 30°C (59°F to 86°F) [see USP Controlled Room Temperature]. Protect from light.

17 PATIENT COUNSELING INFORMATION

Hypersensitivity Reactions

Advise the patient concerning the risk of hypersensitivity reactions that can occur both during and after ULTRAVIST administration. Advise the patient to report any signs or symptoms of hypersensitivity reactions during the procedure and to seek immediate medical attention for any signs or symptoms experienced after discharge [see Warnings and Precautions (5.2)].

Advise patients to inform their physician if they develop a rash after receiving ULTRAVIST [see Warnings and Precautions (5.11)]

Acute Kidney Injury

Advise the patient concerning appropriate hydration to decrease the risk of contrast induced kidney injury [see Warnings and Precautions (5.3)].

Extravasation

If extravasation occurs during injection, advise patients to seek medical care for progression of symptoms [see Warnings and Precautions (5.6)].

Thyroid Dysfunction

Advise parents/caregivers about the risk of developing thyroid dysfunction after ULTRAVIST administration. Advise parents/caregivers about when to seek medical care for their child to monitor for thyroid function [see Warnings and Precautions (5.8)].

Lactation

Advise lactating women that interruption of breast feeding is not necessary, however, to avoid any exposure a lactating woman may consider pumping and discarding breast milk for 12 to 24 hours after ULTRAVIST administration [see Use in Specific Populations (8.2)].

Manufactured for:

Bayer HealthCare Pharmaceuticals Inc.
  Whippany, NJ 07981
Manufactured in Germany

©1995, Bayer HealthCare Pharmaceuticals Inc. All rights reserved.

The following are representative examples of ULTRAVIST labeling. See the "How Supplied" section for a complete listing of all components.

Package/Label Display Panel 240mg Iodine per 50mL

NDC 50419-342-05 50 mL

sterile solution

Ultravist®

(brand of iopromide)

240 mgI/mL injection

Rx only

Single-dose container

Discard unused portion.

NOT FOR INTRATHECAL USE

Dose: See package insert. For intravascular use only. Each mL contains 498.72 mg iopromide with 2.42 mg tromethamine as a buffer and 0.1 mg edetate calcium disodium as a stabilizer.

Contains no antimicrobial preservative.
Protect from light.

Store at 25°C (77°F); excursions permitted to 15-30°C (59-86°F).

Mfd. for:

Bayer HealthCare Pharmaceuticals Inc.

Wayne, NJ 07470

Mfd in Germany

50 mL

240

Package/Label Display Panel 300 mg Iodine per 50mL

NDC 50419-344-05 50 mL

sterile solution

Ultravist®

(brand of iopromide)

300 mgI/mL injection

Rx only

Single-dose container

Discard unused portion.

NOT FOR INTRATHECAL USE

Dose: See package insert. For intravascular use only. Each mL contains 623.4 mg iopromide with 2.42 mg tromethamine as a buffer and 0.1 mg edetate calcium disodium as a stabilizer.

Contains no antimicrobial preservative.
Protect from light.

Store at 25°C (77°F); excursions permitted to 15-30°C (59-86°F).

Mfd. for:

Bayer HealthCare Pharmaceuticals Inc.

Wayne, NJ 07470

Mfd in Germany

50 mL

300

Package/Label Display Panel 370 mg Iodine per 50mL

NDC 50419-346-05 50 mL

sterile solution

Ultravist®

(brand of iopromide)

370 mgI/mL injection

Rx only

Single-dose container

Discard unused portion.

NOT FOR INTRATHECAL USE

Dose: See package insert. For intravascular use only. Each mL contains 768.86 mg iopromide with 2.42 mg tromethamine as a buffer and 0.1 mg edetate calcium disodium as a stabilizer.

Contains no antimicrobial preservative.
Protect from light.

Store at 25°C (77°F); excursions permitted to 15-30°C (59-86°F).

Mfd. for:

Bayer HealthCare Pharmaceuticals Inc.

Wayne, NJ 07470

Mfd in Germany

Bayer

50 mL

370

PACKAGE/LABEL PRINCIPAL DISPLAY PANEL

NDC 50419-342-21 200 mL

sterile solution

pharmacy bulk package

not for direct infusion

Ultravist®

(brand of iopromide)s

240 mg Iodine per mL

injection

Rx only

NOT FOR INTRATHECAL USE

Discard unused portion 10 hours after initial puncture of the container.

Dose: See package insert. For intravascular use only.

Each mL contains 498.72 mg iopromide with 2.42 mg tromethamine as a buffer and 0.1 mg edetate calcium disodium as a stabilizer.

Contains no antimicrobial preservative.
Protect from light.

Store at 25°C (77°F); excursions permitted to 15-30°C (59-86°F).

Mfd. for:

Bayer HealthCare Pharmaceuticals Inc.

Wayne, NJ 07470

Mfd in Germany

200 mL

240

PRINCIPAL DISPLAY PANEL - 500 mL Bottle Package Label

BAYER

- 300 mg
  Iodine per
  mL injection
- 8 x 500 mL
  each
- injection

NDC 50419-344-65
sterile solution

imaging bulk package
not for direct infusion

Ultravist®
(Iopromide)
injection
300 mg Iodine per mL

For Intravenous
Use Only

For use only with an automated
contrast injection system, contrast
management system, or contrast
media transfer set approved or
cleared for use with this contrast
agent in this Imaging Bulk Package

Discard 10 hours after initial puncture.

Recommended Dosage:
See Prescribing Information.

Not For Intrathecal Use

See drug and device labeling for
information on devices indicated for
use with this Imaging Bulk Package
and techniques to help assure safe use

Each mL contains 623.4 mg iopromide,
with 2.42 mg tromethamine as a buffer,
0.1 mg edetate calcium disodium as a
stabilizer, and sodium hydroxide and
hydrochloric acid for pH adjustment.

Contains no antimicrobial preservative.

Store at 25°C (77°F); excursions
permitted to 15° to 30°C (59° to 86°F)
[see USP Controlled Room Temperature].
Protect from light.

Rx only

500 mL
300

LOT

EXP

89535379

Mfd. for:
Bayer HealthCare
Pharmaceuticals Inc.
Whippany, NJ 07981
Mfd. in Germany

Bayer

PACKAGE/LABEL PRINCIPAL DISPLAY PANEL

NDC 50419-346-58 8 x 500 mL

sterile solution

Pharmacy bulk package

not for direct infusion

Ultravist®

(brand of iopromide)

370 mg Iodine per mL

injection

Rx only